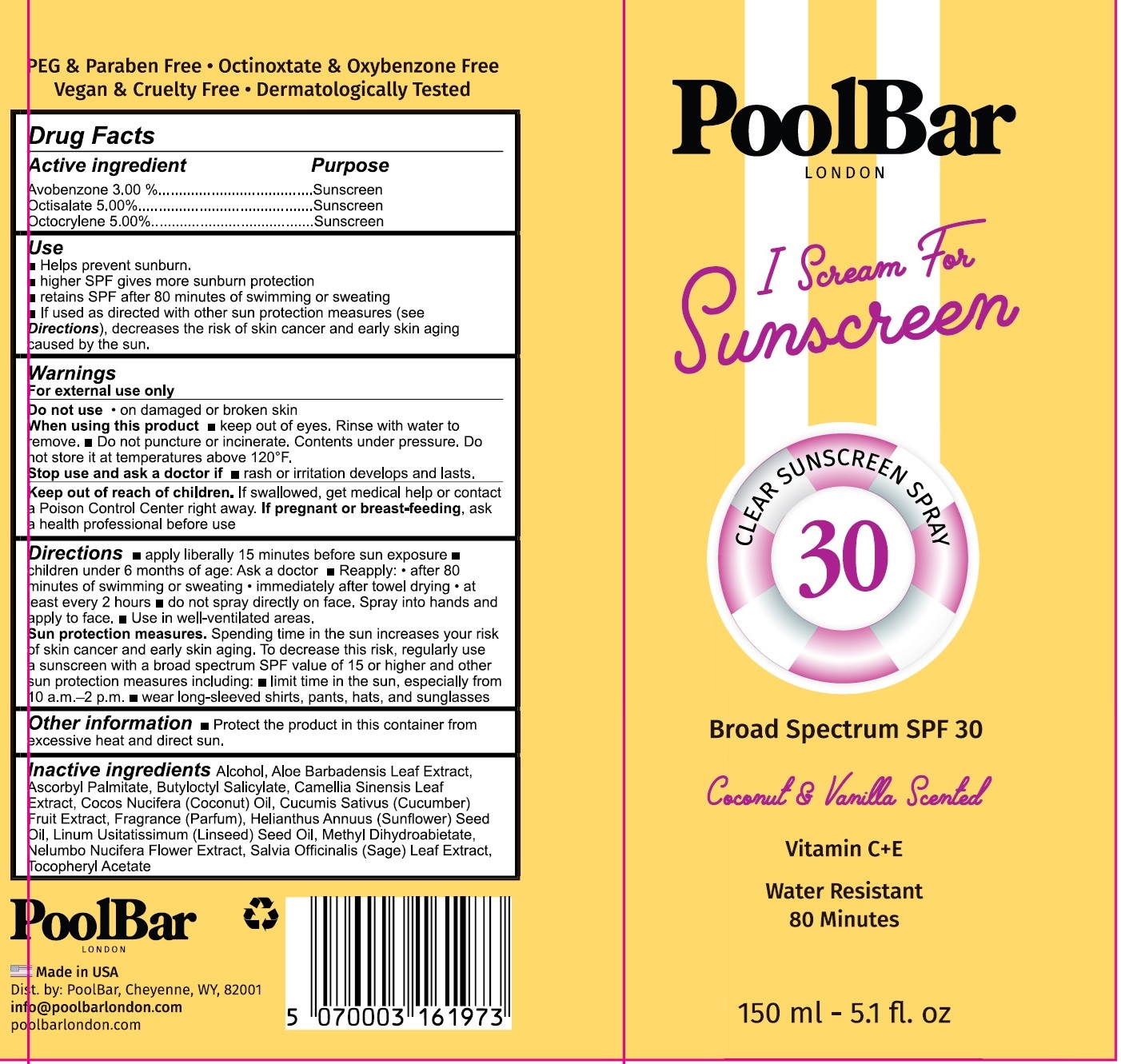 DRUG LABEL: PoolBar I Scream For Sunscreen SPF 30 Coconut and Vanilla
NDC: 84953-873 | Form: LIQUID
Manufacturer: POOLBAR
Category: otc | Type: HUMAN OTC DRUG LABEL
Date: 20250806

ACTIVE INGREDIENTS: AVOBENZONE 30 mg/1 mL; OCTISALATE 50 mg/1 mL; OCTOCRYLENE 50 mg/1 mL
INACTIVE INGREDIENTS: ALCOHOL; ALOE VERA LEAF; ASCORBYL PALMITATE; BUTYLOCTYL SALICYLATE; GREEN TEA LEAF; COCONUT OIL; CUCUMBER; SUNFLOWER OIL; LINSEED OIL; METHYL DIHYDROABIETATE; NELUMBO NUCIFERA FLOWER; SAGE; .ALPHA.-TOCOPHEROL ACETATE

PoolBar I Scream For Sunscreen SPF 30 Coconut and Vanilla

Active ingredient

Avobenzone 3.00%
Octisalate 5.00%
Octocrylene 5.00%

Purpose

Sunscreen

Use

- Helps prevent sunburn.
- higher SPF gives more sunburn protection
- retains SPF after 80 minutes of swimming or sweating
- If used as directed with other sun protection measures (see Directions), decreases the risk of skin cancer and early skin aging caused by the sun.

Warnings

For external use only

Do not use

- on damaged or broken skin

When using this product

- keep out of eyes. Rinse with water to remove.
- Do not puncture or incinerate. Contents under pressure. Do not store it at temperatures above 120ºF.

Stop use and ask a doctor if

- rash or irritation develops and lasts.

Keep out of reach of children.

If swallowed, get medical help or contact a Poison Control Center right away.

If pregnant or breast-feeding,

ask a health professional before use

Directions

- apply liberally 15 minutes before sun exposure
- children under 6 months of age: Ask a doctor.
- Reapply:
- after 80 minutes of swimming or sweating
- immediately after towel drying
- at least every 2 hours
- do not spray directly on face. Spray into hands and apply to face.
- Use in well-ventilated areas.
- Sun protection measures.Spending time in the sun increases your risk of skin cancer and early skin aging. To decrease the risk, regularly use a sunscreen with broad spectrum SPF value of 15 or higher and other sun protection measures including:
- limit time in the sun, especially from 10 a.m.-2 p.m.
- wear long-sleeved shirts, pants, hats, and sunglasses

Other information

- Protect the product in this container from excessive heat and direct sun.

Inactive ingredients

Alcohol, Aloe Barbadensis Leaf Extract, Ascorbyl Palmitate, Butyloctyl Salicylate, Camellia Sinensis Leaf Extract, Cocos Nucifera (Coconut) Oil, Cucumis Sativus (Cucumber) Fruit Extract, Fragrance (Parfum), Helianthus Annuus (Sunflower) Seed Oil, Linum Usitatissum (Linseed) Seed Oil, Methyl Dihydroabietate, Nelumbo Nucifera Flower Extract, Salvia Officinalis (Sage) Leaf Extract, Tocopheryl Acetate